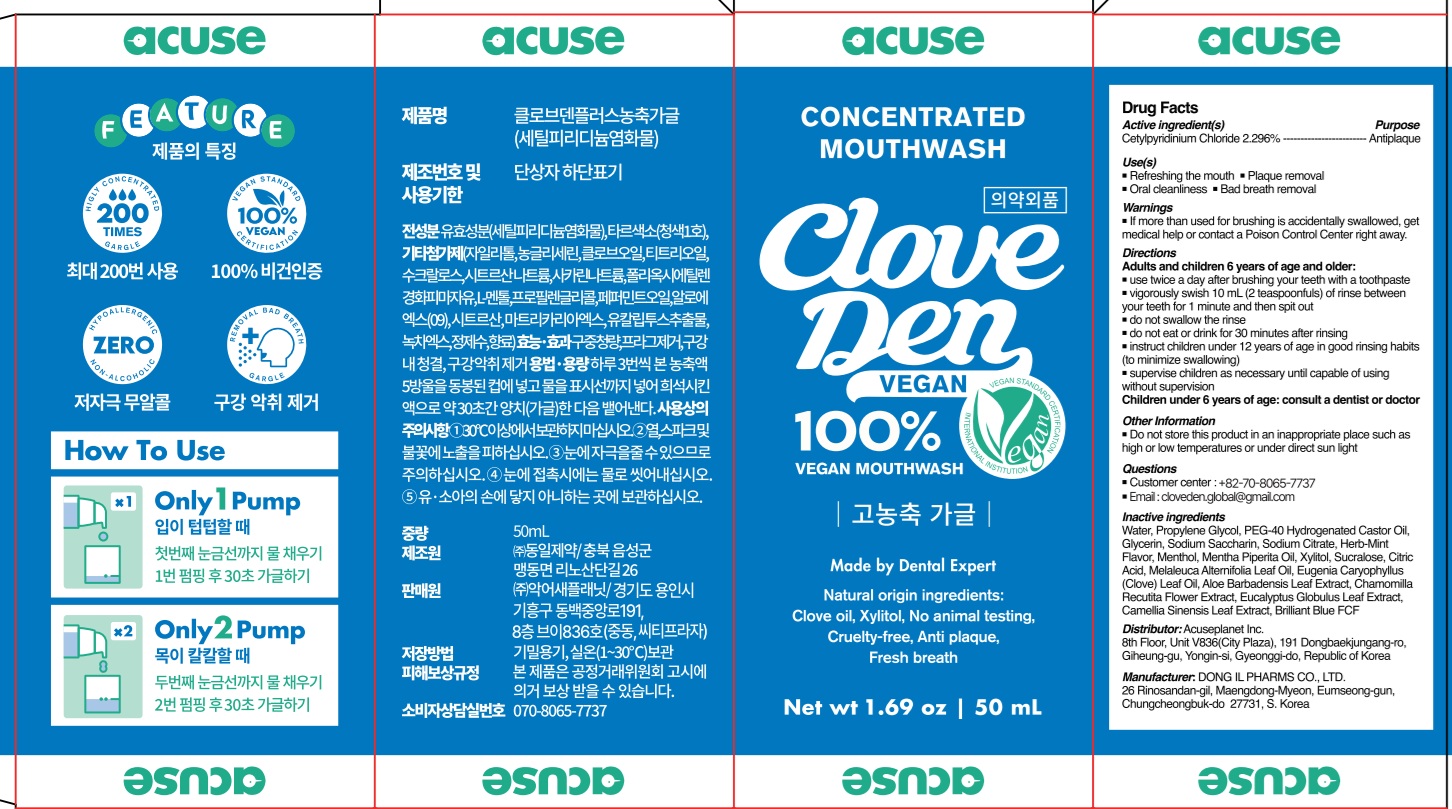 DRUG LABEL: Cloveden 100 times higher concentrated
NDC: 73242-1115 | Form: MOUTHWASH
Manufacturer: DONG IL PHARMS CO.,LTD
Category: otc | Type: HUMAN OTC DRUG LABEL
Date: 20250926

ACTIVE INGREDIENTS: CETYLPYRIDINIUM CHLORIDE 2.29 g/100 mL
INACTIVE INGREDIENTS: WATER; PROPYLENE GLYCOL; GLYCERIN; PEG-40 HYDROGENATED CASTOR OIL

Active ingredient(s)

Cetylpyridinium Chloride 2.296%

Purpose

Antiplaque

INDICATIONS AND USAGE

Use(s)

■ Refreshing the mouth

■ Plaque removal

■ Oral cleanliness

■ Bad breath removal

Warnings

■ If more than used for brushing is accidentally swallowed, get medical help or contact a Poison Control Center right away.

Keep out of reach of children

Directions

Adults and children 6 years of age and older:

■ use twice a day after brushing your teeth with a toothpaste

■ vigorously swish 10 mL (2 teaspoonfuls) of rinse between your teeth for 1 minute and then spit out

■ do not swallow the rinse

■ do not eat or drink for 30 minutes after rinsing

■ instruct children under 12 years of age in good rinsing habits (to minimize swallowing)

■supervise children as necessary until capable of using without supervision

Children under 6 years of age: consult a dentist or doctor

Other Information

■ Do not store this product in an inappropriate place such as high or low temperatures or under direct sun light

Questions

■ https://acuseplanet.cafe24.com/shop2/
■ Customer center : 82-70-8065-7737

Inactive ingredients

Water, Propylene Glycol, PEG-40 Hydrogenated Castor Oil, Glycerin, Sodium Saccharin, Sodium Citrate, Herb-Mint Flavor, Menthol, Mentha Piperita Oil, Xylitol, Sucralose, Citric Acid, Melaleuca Alternifolia Leaf Oil, Eugenia Caryophyllus (Clove) Leaf Oil, Aloe Barbadensis Leaf Extract, Chamomilla Recutita Flower Extract, Eucalyptus Globulus Leaf Extract, Camellia Sinensis Leaf Extract, Brilliant Blue FCF